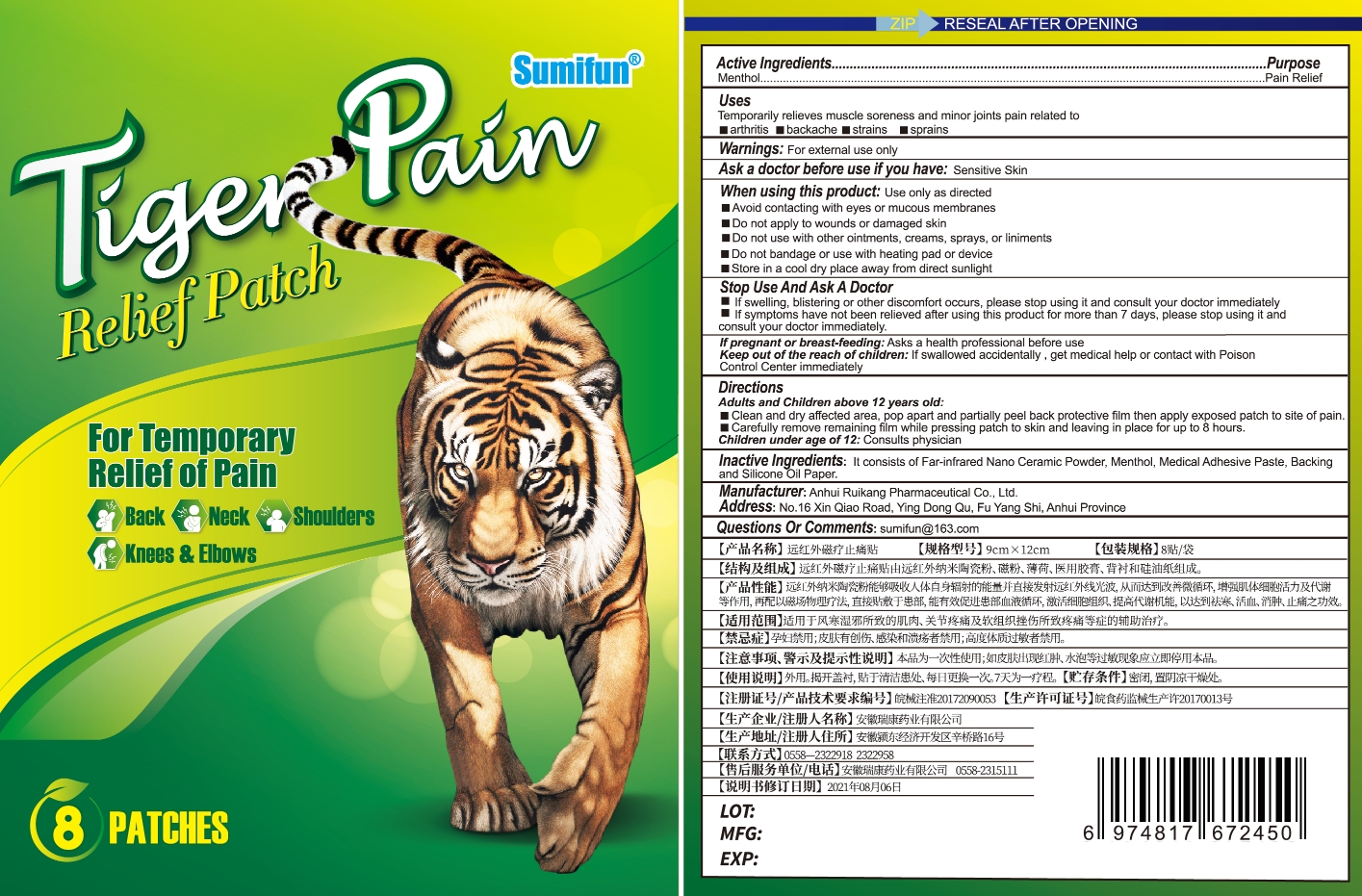 DRUG LABEL: Tiger Pain Relief Patch
NDC: 83675-012 | Form: PATCH
Manufacturer: Guangzhou Hanhai Trading Co., Ltd
Category: otc | Type: HUMAN OTC DRUG LABEL
Date: 20230920

ACTIVE INGREDIENTS: MENTHOL 19 g/100 1
INACTIVE INGREDIENTS: BACKHOUSIA MYRTIFOLIA WHOLE; DIMETHICONOL/TRIMETHYLSILOXYSILICATE CROSSPOLYMER (40/60 W/W; 1000000 PA.S); IVERMECTIN; POWDERED CELLULOSE

Active Ingredient

Menthol 19.0%

Purpose

Pain Relief

Use

Temporarily relieves muscle soreness and minor joints pain related to arthritis, backache, strains, sprains

Warnings

For external use only. Do not take it internally.

Keep Out Of Reach Of Children
Sensitive Skin

Do not use

Product shall not be eat

When Using

Use only as directedAvoid contacting with eyes or mucous membranesDo not apply to wounds or damaged skinDo not use with other ointments, creams, sprays, or linimentsDo not bandage or use with heating pad or devictStore in a cool dry place away from direct sunlight

Stop Use

In case of adverse reactions, please stop using this product.If the symptoms.

Ask Doctor

ask doctor in case of Sensitive Skin

Keep Oot Of Reach Of Children

Keep Out Of Reach Of Children

Directions

Take one piece of this product when needed, remove the waxpaper,

stick to the desired area and press the surrounding, replace it every 8 hours.

Children should be used under adult supervision.

Other information

Store the product in a cool, dry and well-ventilated place

Avoid direct sunlight

Inactive ingredients

Far-infrared Nano Ceramic Powder,

Medical Adhesive Paste,

Backing

Silicone Oil Paper